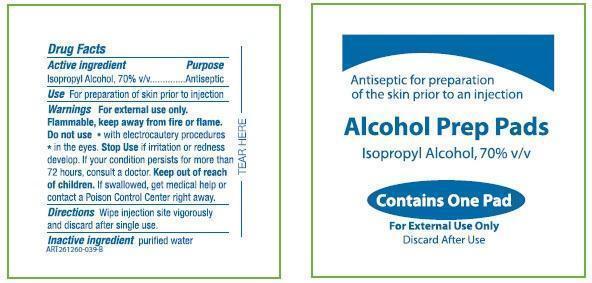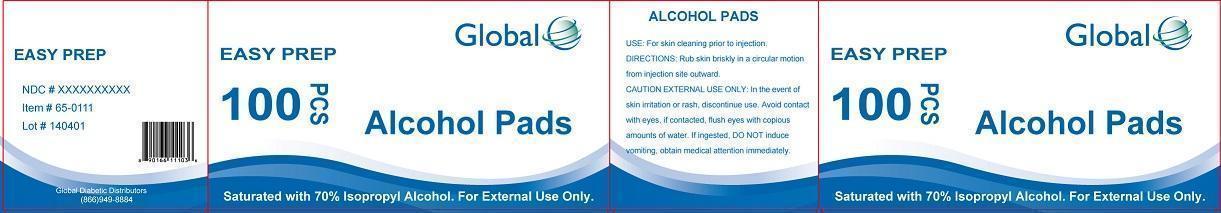 DRUG LABEL: Global EASY PREP alcohol prep pads
NDC: 89156-000 | Form: LIQUID
Manufacturer: Global Diabetic Distributors
Category: otc | Type: HUMAN OTC DRUG LABEL
Date: 20241218

ACTIVE INGREDIENTS: ISOPROPYL ALCOHOL 70 g/100 g
INACTIVE INGREDIENTS: WATER

Global EASY PREP alcohol prep pads

Active Ingredient

Isopropyl Alcohol USP, 70% v/v

Purpose

Antiseptic

Use

For preparation of the skin prior to injection

Warnings

For external use only.
Flammable, keep away from fire or flame.
Do not use

- with electrocautery procedures
- in the eyes

Stop use if irritation or redness develop. If your condition persists for more than 72 hours, consult a doctor.

Keep out of reach of Children

If swallowed, get medical help or contact a Poison Control Center immediately.

Directions

Wipe injection site vigorously and discard after single use.

Inactive Ingredients:

purified water